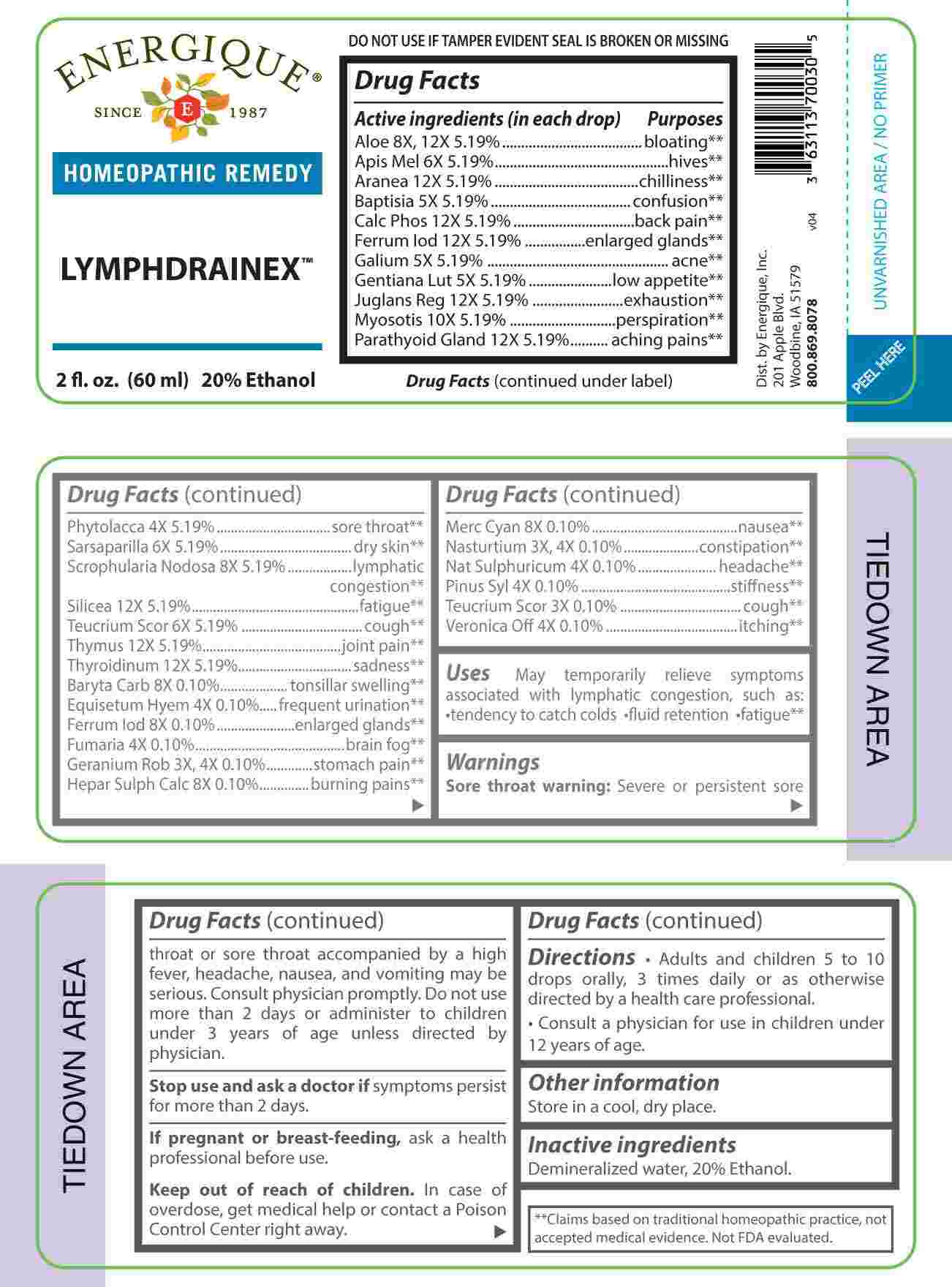 DRUG LABEL: Lymphdrainex
NDC: 44911-0689 | Form: LIQUID
Manufacturer: Energique, Inc.
Category: homeopathic | Type: HUMAN OTC DRUG LABEL
Date: 20231228

ACTIVE INGREDIENTS: GERANIUM ROBERTIANUM WHOLE 3 [hp_X]/1 mL; NASTURTIUM OFFICINALE 3 [hp_X]/1 mL; TEUCRIUM SCORODONIA FLOWERING TOP 3 [hp_X]/1 mL; EQUISETUM HYEMALE WHOLE 4 [hp_X]/1 mL; FUMARIA OFFICINALIS FLOWERING TOP 4 [hp_X]/1 mL; SODIUM SULFATE 4 [hp_X]/1 mL; PHYTOLACCA AMERICANA ROOT 4 [hp_X]/1 mL; PINUS SYLVESTRIS LEAFY TWIG 4 [hp_X]/1 mL; VERONICA OFFICINALIS FLOWERING TOP 4 [hp_X]/1 mL; BAPTISIA TINCTORIA ROOT 5 [hp_X]/1 mL; GALIUM APARINE WHOLE 5 [hp_X]/1 mL; GENTIANA LUTEA ROOT 5 [hp_X]/1 mL; APIS MELLIFERA 6 [hp_X]/1 mL; SMILAX ORNATA ROOT 6 [hp_X]/1 mL; BARIUM CARBONATE 8 [hp_X]/1 mL; CALCIUM SULFIDE 8 [hp_X]/1 mL; MERCURIC CYANIDE 8 [hp_X]/1 mL; SCROPHULARIA NODOSA WHOLE 8 [hp_X]/1 mL; ALOE 8 [hp_X]/1 mL; FERROUS IODIDE 8 [hp_X]/1 mL; MYOSOTIS ARVENSIS WHOLE 10 [hp_X]/1 mL; ARANEUS DIADEMATUS 12 [hp_X]/1 mL; TRIBASIC CALCIUM PHOSPHATE 12 [hp_X]/1 mL; JUGLANS REGIA FRUIT RIND, IMMATURE 12 [hp_X]/1 mL; JUGLANS REGIA LEAF 12 [hp_X]/1 mL; BOS TAURUS PARATHYROID GLAND 12 [hp_X]/1 mL; SILICON DIOXIDE 12 [hp_X]/1 mL; SUS SCROFA THYMUS 12 [hp_X]/1 mL; THYROID 12 [hp_X]/1 mL
INACTIVE INGREDIENTS: WATER; ALCOHOL

DRUG FACTS:

ACTIVE INGREDIENTS:

(in each drop) Aloe 8X, 12X 5.19%, Apis Mellifica 6X 5.19%, Aranea Diadema 12X 5.19%, Baptisia Tinctoria 5X 5.19%, Calcarea Phosphorica 12X 5.19%, Ferrum Iodatum 12X 5.19%, Galium Aparine 5X 5.19%, Gentiana Lutea 5X 5.19%, Juglans Regia 12X 5.19%, Myosotis Arvensis 10X 5.19%, Parathyroid Gland 12X 5.19%, Phytolacca Decandra 4X 5.19%, Sarsaparilla 6X 5.19%, Scrophularia Nodosa 8X 5.19%, Silicea 12X 5.19%, Teucrium Scorodonia 6X 5.19%, Thymus 12X 5.19%, Thyroidinum 12X 5.19%, Baryta Carbonica 8X 0.10%, Equisetum Hyemale 4X 0.10%, Ferrum Iodatum 8X 0.10%, Fumaria Officinalis 4X 0.10%, Geranium Robertianum 3X, 4X 0.10%, Hepar Sulphuris Calcareum 8X 0.10%, Mercurius Cyanatus 8X 0.10%, Nasturtium Aquaticum 3X, 4X 0.10%, Natrum Sulphuricum 4X 0.10%, Pinus Sylvestris 4X 0.10%, Teucrium Scorodonia 3X 0.10%, Veronica Officinalis 4X 0.10%.

PURPOSE:

Aloe - bloating,** Apis Mellifica - hives,** Aranea Diadema - chilliness,** Baptisia Tinctoria - confusion,** Calcarea Phosphorica – back pain,** Ferrum Iodatum – enlarged glands,** Galium Aparine - acne,** Gentiana Lutea – low appetite,** Juglans Regia - exhaustion,** Myosotis Arvensis - perspiration,** Parathyroid Gland – aching pains,** Phytolacca Decandra – sore throat,** Sarsaparilla – dry skin,** Scrophularia Nodosa – lymphatic congestion,** Silicea - fatigue,** Teucrium Scorodonia - cough,** Thymus – joint pain,** Thyroidinum - sadness,** Baryta Carbonica – tonsillar swelling,** Equisetum Hyemale – frequent urination,** Fumaria Officinalis – brain fog,** Geranium Robertianum – stomach pain,** Hepar Sulphuris Calcareum – burning pains,** Mercurius Cyanatus - nausea,** Nasturtium Aquaticum - constipation,** Natrum Sulphuricum - headache,** Pinus Sylvestris - stiffness,** Veronica Officinalis – itching.**
**Claims based on traditional homeopathic practice, not accepted medical evidence. Not FDA evaluated.

USES:

May temporarily relieve symptoms associated with lymphatic congestion, such as: • tendency to catch colds • fluid retention • fatigue.**
**Claims based on traditional homeopathic practice, not accepted medical evidence. Not FDA evaluated.

WARNINGS:

Sore throat warning:Severe or persistent sore throat or sore throat accompanied by a high fever, headache, nausea, and vomiting may be serious. Consult physician promptly. Do not use more than 2 days or administer to children under 3 years of age unless directed by physician.
Stop use and ask a doctor if symptoms persist for more than 2 days.

If pregnant or breast-feeding, ask a health professional before use.
Keep out of reach of children. In case of overdose, get medical help or contact a Poison Control Center right away.

DO NOT USE IF TAMPER EVIDENT SEAL IOS BROKEN OR MISSING

Store in a cool, dry place.

KEEP OUT OF REACH OF CHILDREN:

In case of overdose, get medical help or contact a Poison Control Center right away.

DIRECTIONS:

• Adults and children 5 to 10 drops orally, 3 times daily or as otherwise directed by a health care professional. • Consult a physician for use in children under 12 years of age.

INACTIVE INGREDIENTS:

Demineralized water, 20% Ethanol.

QUESTIONS:

Dist. by Energique, Inc.

201 Apple Blvd.

Woodbine, IA 51579

800.869.8078

PACKAGE LABEL DISPLAY:

ENERGIQUE
SINCE 1987
HOMEOPATHIC REMEDY

LYMPHDRAINEX

2 fl. oz. (60 ml)